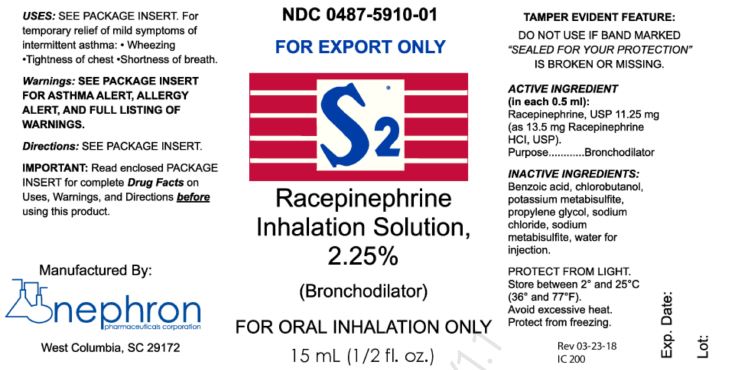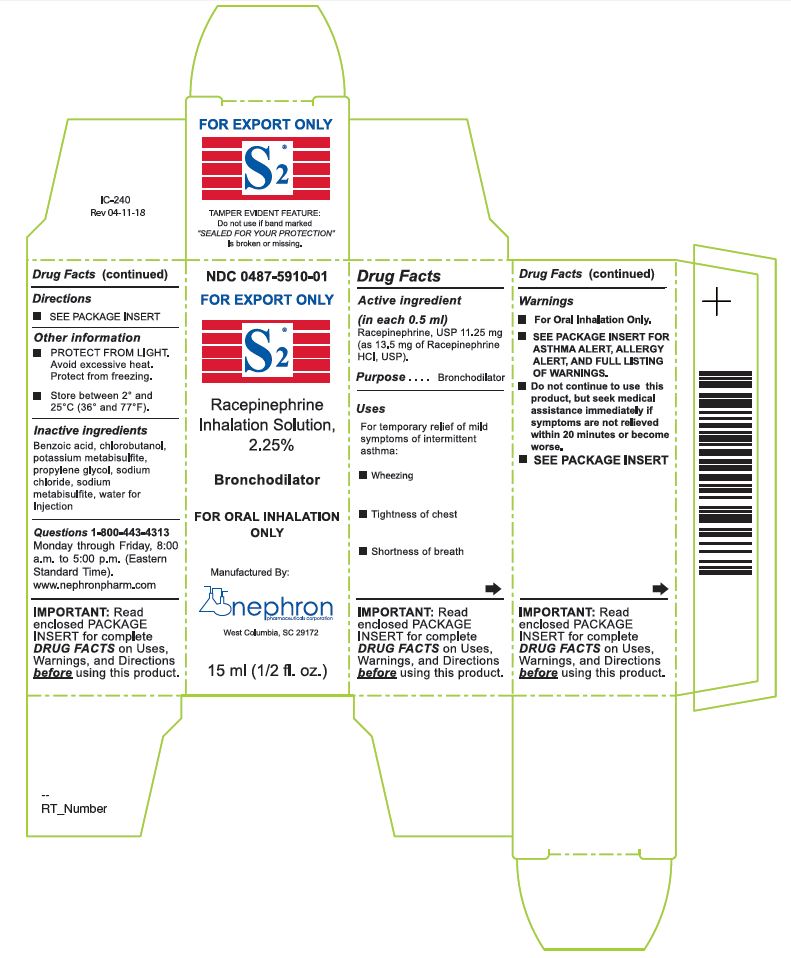 DRUG LABEL: S2 Racepinephrine
NDC: 0487-5910 | Form: SOLUTION
Manufacturer: Nephron SC, Inc.
Category: otc | Type: HUMAN OTC DRUG LABEL
Date: 20241219

ACTIVE INGREDIENTS: RACEPINEPHRINE HYDROCHLORIDE 11.25 mg/0.5 mL
INACTIVE INGREDIENTS: BENZOIC ACID; CHLOROBUTANOL; POTASSIUM METABISULFITE; PROPYLENE GLYCOL; SODIUM CHLORIDE; SODIUM METABISULFITE; WATER

Racepinephrine Inhalation Solution, USP 2.25% (For Export Only)

Drug Facts

Active ingredient (in each 0.5 ml)

Racepinephrine, USP 11.25 mg (as 13.5 mg of Racepinephrine HCl, USP).

Purpose

Bronchodilator

Uses

For temporary relief of mild symptoms of intermittent asthma:

- Wheezing
- Tightness of chest
- Shortness of breath

Warnings

Asthma alert

Because asthma may be life threatening, see a doctor if you:

- Are not better in 20 minutes
- Get worse
- Need more than 12 inhalations in 24 hours
- Use more than 9 inhalations in 24 hours for 3 or more days a week
- Have more than 2 asthma attacks in a week

These may be signs that your asthma is getting worse.

Allergy alert

Contains potassium metabisulfite and sodium metabisulfite, sulfites that may cause allergic-type reactions including anaphylactic symptoms and life-threatening or less severe asthmatic episodes in certain susceptible people. The overall prevalence of sulfite sensitivity in the general population is unknown and probably low. Sulfite sensitivity is seen more frequently in asthmatic than in nonasthmatic people.

Do not use

- Unless a doctor said you have asthma
- If you are now taking a prescription monoamine oxidase inhibitor (MAOI) (certain drugs for depression, psychiatric, or emotional conditions, or Parkinson's disease), or for 2 weeks after stopping the MAOI drug. If you do not know if your prescription drug contains a MAOI, ask a doctor or pharmacist before taking this product.
- If product is brown in color or cloudy

Ask a doctor before use if you have

- Ever been hospitalized for asthma
- Heart disease
- High blood pressure
- Diabetes
- Thyroid disease
- Seizures
- Narrow angle glaucoma
- A psychiatric or emotional condition
- Trouble urinating due to an enlarged prostate gland

Ask a doctor or pharmacist before use if you are

- Taking prescription drugs for asthma, obesity, weight control, depression, or psychiatric or emotional conditions.
- Taking any drug that contains phenylephrine, pseudoephedrine, ephedrine, or caffeine (such as for allergy, cough-cold, or pain).

Stop use and ask a doctor if

- Your asthma is getting worse (See Asthma alert)
- You have difficulty sleeping
- You have a rapid heartbeat
- You have tremors, nervousness, or seizure

When using this product

Your blood pressure or heart rate may go up. This could increase your risk of heart attack or stroke, which may cause death.

- Your risk of heart attack or stroke increases if you:
  - Have a history of high blood pressure or heart disease
  - Take this product more frequently or take more than the recommended dose.
  - Avoid foods or beverages that contain caffeine
  - Avoid dietary supplements containing ingredients reported or claimed to have a stimulant effect.

PREGNANCY OR BREAST FEEDING

- If pregnant or breast-feeding, ask a health professional before use.

- Keep out of reach of children. In case of overdose, get medical help or contact a Poison Control Center right away.

Directions

- Do not use more than directed
- The ingredient is used in an aqueous solution at a concentration equivalent to 1 percent epinephrine.
- For use in a nebulizer:
  Add 0.5 ml (approximately 10 drops) of solution to nebulizer.
- Adults and children 4 years of age and over:
  1 to 3 inhalations not more often than every 3 hours. Start with one inhalation, then wait at least 1 minute. If symptoms do not improve, use once more. Do not exceed more than 3 inhalations over a 3 hour period.
  Do not use more than 12 inhalations in 24 hours.
  The use of this product by children should be supervised by an adult.
- Children under 4 years of age: ask a doctor.

Other Information

- Protect from light. Avoid excessive heat. Protect from freezing.
- Store between 2°C and 25°C (36°F and 77°F).
- How Supplied: S2® Racepinephrine Inhalation Solution, 2.25% is supplied in 15 ml amber glass, multi-dose bottles.
  NDC 0487-5910-01 15 ml amber glass, multi-dose bottle

Inactive Ingredients

Benzoic acid, chlorobutanol, potassium metabisulfite, propylene glycol, sodium chloride, sodium metabisulfite, water for injection.

Questions?

1-800-443-4313

Monday through Friday, 8:00 a.m. to 5:00 p.m. (Eastern Standard Time).

Manufactured By:
Nephron Pharmaceuticals Corporation

West Columbia, SC 29172

PRINCIPAL DISPLAY PANEL - 15 ml Bottle

Principal Dispay - Primary Container Label (15 mL Amber Glass, Multi-Dose Bottle)

NDC 0487-5910-01

Principal Display - Carton (Individual 15 mL Amber Glass, Multi-Dose Bottle)

NDC 0487-5910-01